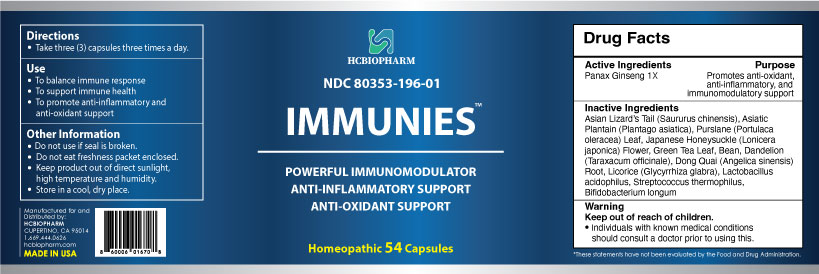 DRUG LABEL: Immunies
NDC: 80353-196 | Form: CAPSULE
Manufacturer: HCBIOPHARM LLC
Category: homeopathic | Type: HUMAN OTC DRUG LABEL
Date: 20250103

ACTIVE INGREDIENTS: PANAX GINSENG WHOLE 1 [hp_X]/1 1
INACTIVE INGREDIENTS: SAURURUS CHINENSIS WHOLE; PLANTAGO ASIATICA; LONICERA JAPONICA FLOWER; GREEN TEA LEAF; BEAN; TARAXACUM OFFICINALE; PORTULACA OLERACEA LEAF; ANGELICA SINENSIS ROOT; GLYCYRRHIZA GLABRA

Active Ingredient

Panax Ginseng 1X

Purpose

Promotes anti-oxidant, anti-inflammatory, and immunomodulatory support

Keep Out of Reach of Children

Directions

Take three (3) capsules three times a day.

Use

- To balance immune response
- To support immune health
- To promote anti-inflammatory, and anti-oxidant support

Inactive Ingredients

Asian Lizard’s Tail (Saururus chinensis), Asiatin Plantain (Plantago asiatica), Purslane (Portulaca oleracea) Leaf, Japanese Honeysuckle (Lonicera japonica) Flower, Green Tea Leaf, Bean, Dandelion (Taraxacum officinale), Dong Quai (Angelica sinensis)

Root, Licorice (Glycyrrhiza glabra), Lactobacillus acidophilus, Streptococcus Thermophilus, Bifidobacterium longum

Warning

Individuals with known medical conditions should consult a doctor prior to using this.

Other Information

- Do not use if seal is broken.
- Do not eat freshness packet enclosed.
- Keep product out of direct sunlight, high temperature, and humidity.
- Store in a cool, dry place.

Package Label Display

Immunies

Powerful Immunomodulator

Anti-Inflammatory Support

Anti-Oxidant Support

Homeopathic 54 Capsules